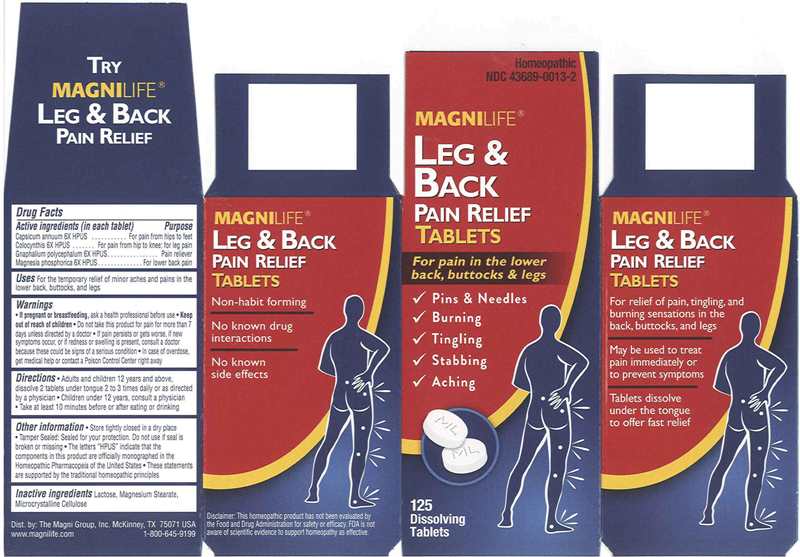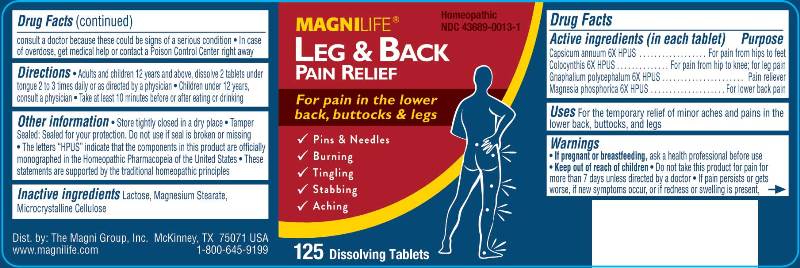 DRUG LABEL: Leg and Back Pain Relief
NDC: 43689-0013 | Form: TABLET
Manufacturer: The Magni Company
Category: homeopathic | Type: HUMAN OTC DRUG LABEL
Date: 20200914

ACTIVE INGREDIENTS: CAPSICUM 6 [hp_X]/1 1; CITRULLUS COLOCYNTHIS FRUIT PULP 6 [hp_X]/1 1; PSEUDOGNAPHALIUM OBTUSIFOLIUM 6 [hp_X]/1 1; MAGNESIUM PHOSPHATE, DIBASIC TRIHYDRATE 6 [hp_X]/1 1
INACTIVE INGREDIENTS: LACTOSE; MAGNESIUM STEARATE; CELLULOSE, MICROCRYSTALLINE

Drug Facts:

ACTIVE INGREDIENTS:

Capsicum Annuum 6X, Colocynthis 6X, Gnaphalium Polycephalum 6X, Magnesia Phosphorica 6X

USES:

For the temporary relief of minor aches and pains in the lower back, buttocks and legs.

WARNINGS:

• If pregnant or breastfeeding, ask a health professional before use

• Keep out of reach of children, Do not take this product for pain for more than 7 days unless directed by a doctor. If pain persists or gets worse, if new symptoms occur, or redness or swelling is present, consult a doctor because these could be signs of a serious condition.

• In case of overdose, get medical help or contact a Poison Control Center right away

OTHER INFORMATION:

• Store tightly closed in a dry place

• Tamper Sealed: Sealed for your protection. Do not use if seal is broken or missing

• The letters "HPUS" indicate that the components in this product are officially monographed in the Homeopathic Pharmacopeia of the United

States

• These statements are supported by the traditional homeopathic principles

DIRECTIONS:

• Adults and children 12 years and above: Dissolve 2 tablets under tongue 2 to 3 times daily or as directed by a physician

• Children under 12: Consult a physician

• Take at least 10 minutes before or after eating or drinking

INACTIVE INGREDIENTS:

Lactose, Magnesium Stearate, Microcrystalline Cellulose

Keep out of reach of children. In case of overdose, get medical help or contact a Poison Control Center right away

INDICATIONS:

For the temporary relief of minor aches and pains in the lower back, buttocks and legs.

QUESTIONS:

Dist. by: The Magni Group, Inc. McKinney, TX 75071 USA

www.magnilife.com 1-800-645-9199

PACKAGE LABEL DISPLAY:

MAGNILIFE Homeopathic

LEG & BACK NDC 43689-0013-1

PAIN RELIEF

For pain in the lower back,

buttocks & legs

√ Pins & Needles

√ Burning

√ Tingling

√ Stabbing

√ Aching

125 Dissolving Tablets